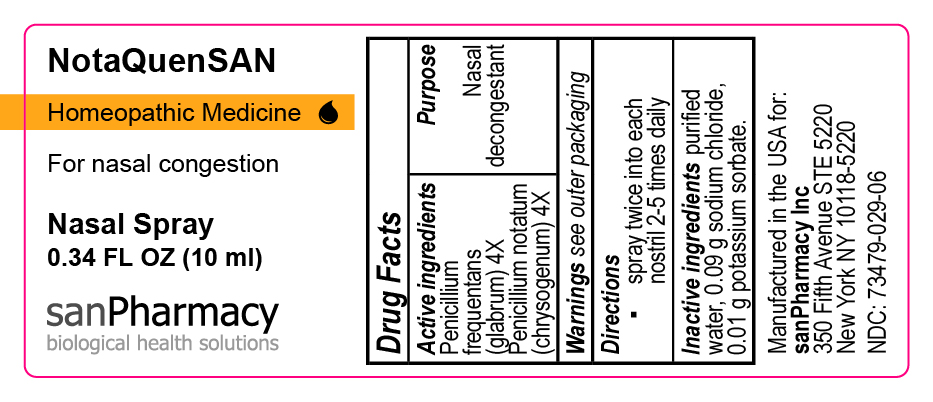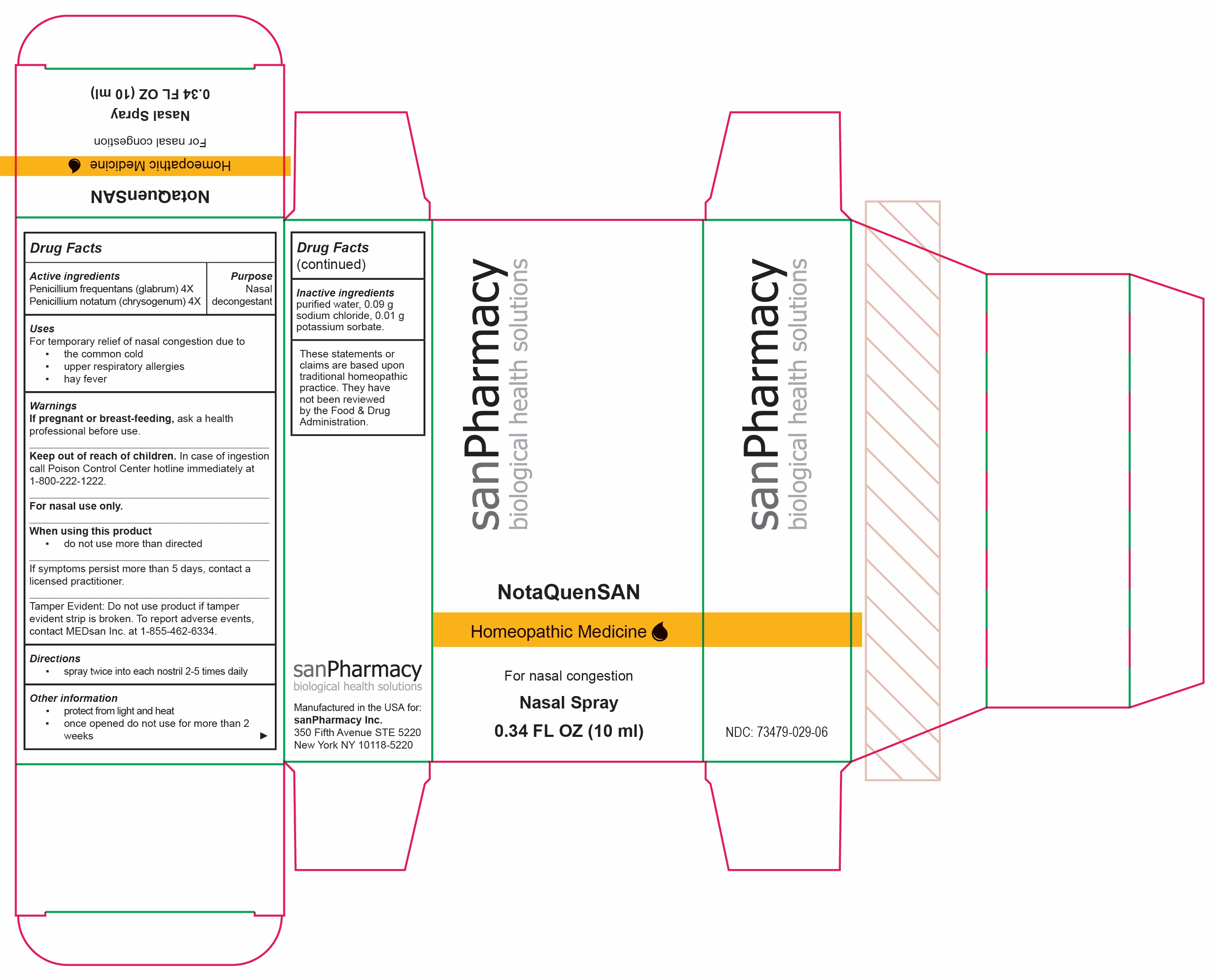 DRUG LABEL: NotaQuenSAN
NDC: 73479-029 | Form: SPRAY
Manufacturer: sanPharmacy Inc.
Category: homeopathic | Type: HUMAN OTC DRUG LABEL
Date: 20231220

ACTIVE INGREDIENTS: PENICILLIUM CHRYSOGENUM VAR. CHRYSOGENUM 4 [hp_X]/10 mL; PENICILLIUM GLABRUM 4 [hp_X]/10 mL
INACTIVE INGREDIENTS: WATER; SODIUM CHLORIDE 0.09 g/10 mL; POTASSIUM SORBATE 0.01 g/10 mL

NotaQuenSAN Nasal Spray

Indications

For temporary relief of nasal congestion due to the common cold, upper respiratory allergies and hay fever.

PURPOSE

Nasal decongestant

Ingredients

Penicillium notatum (chrysogenum) 4X

Penicillium frequentans (glabrum) 4X

INACTIVE INGREDIENT

purified water

0.09g sodium chloride

0.01g potassium sorbate

Dosage

Spray twice into each nostril 2-5 times daily.

Warning

If symptoms persist more than 5 days, contact a licensed practitioner. If pregnant or breast-feeding, ask a health professional before use. Keep out of the reach of children. In case of ingestion call Poison Control Center hotline immediately at 1-800-222-1222. Protect from light and heat.

Keep out of the reach of children.

STORAGE AND HANDLING

Protect from light and heat. Once opened do not use for more than 2 weeks.

Tamper Evident

Do not use product if tamper evident strip is broken. To report adverse events, contact MEDsan Inc. at 1-855-462-6334.

Manufactured in the USA for:
sanPharmacy Inc.
350 Fifth Avenue STE 5220

New York NY 10118-5220

Liability claim

These statements or claims are based upon traditional homeopathic practice. They have not been reviewed by the Food & Drug Administration.

RECENT MAJOR CHANGES

Boxed Warning

Indications and Usage

Warnings and Precautions

PRINCIPAL DISPLAY PANEL - 10 ml Bottle Carton

NotaQuenSAN

Homeopathic
Medicine

For nasal
congestion

0.34 FL OZ
(10ml)

sanPharmacy
biological health solutions